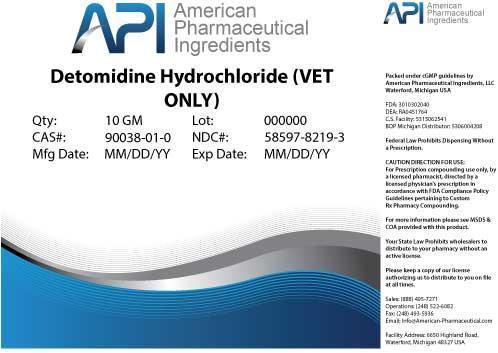 DRUG LABEL: Detomidine Hydrochloride
NDC: 58597-8219 | Form: POWDER
Manufacturer: AMERICAN PHARMACEUTICAL INGREDIENTS LLC
Category: other | Type: BULK INGREDIENT
Date: 20140425

ACTIVE INGREDIENTS: Detomidine Hydrochloride 1 g/1 g

Detomidine Hydrochloride